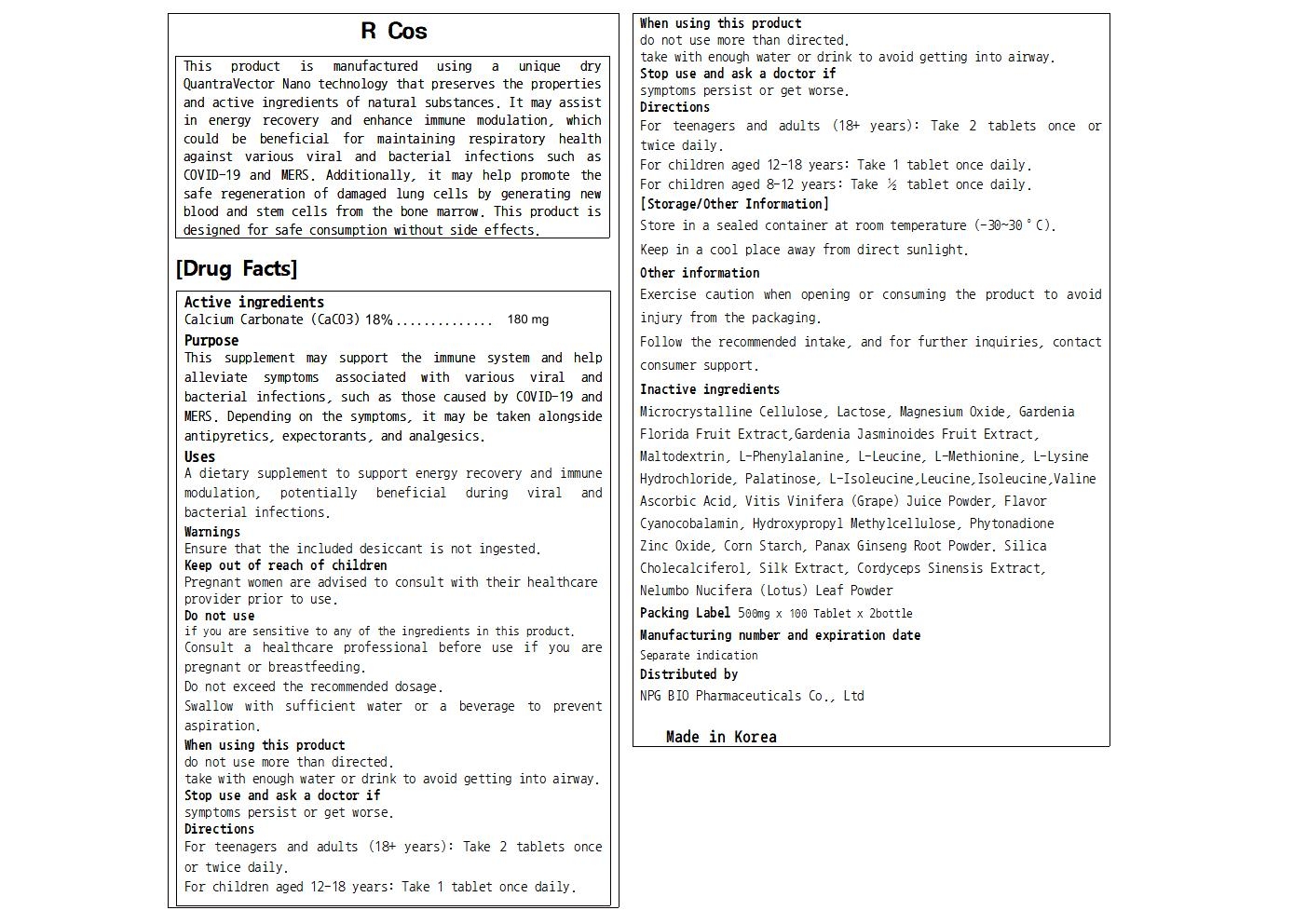 DRUG LABEL: R Cos
NDC: 84540-522 | Form: TABLET
Manufacturer: NPG Bio Pharmaceuticals Co.,Ltd.
Category: otc | Type: HUMAN OTC DRUG LABEL
Date: 20250827

ACTIVE INGREDIENTS: CALCIUM CARBONATE 90 mg/500 mg
INACTIVE INGREDIENTS: OPHIOCORDYCEPS SINENSIS; GARDENIA JASMINOIDES FRUIT; MALTODEXTRIN; LYSINE HYDROCHLORIDE; VALINE; LACTOSE, UNSPECIFIED FORM; BOMBYX MORI FIBER; MAGNESIUM OXIDE; METHIONINE; WINE GRAPE JUICE; CYANOCOBALAMIN; ZINC OXIDE; STARCH, CORN; ISOMALTULOSE ANHYDROUS; ISOLEUCINE; PHYTONADIONE; NELUMBO NUCIFERA LEAF; ASCORBIC ACID; CHOLECALCIFEROL; PHENYLALANINE; ASIAN GINSENG; LEUCINE; MICROCRYSTALLINE CELLULOSE; HYPROMELLOSES; SILICON DIOXIDE

84540-522 R Cos PTP

Active Ingredients

Calcium Carbonate (CaCO3) 18%...............180 mg

Purposes

This supplement may support the immune system and help alleviate symptoms associated with various viral and bacterial infections, such as those caused by COVID-19 and MERS. Depending on the symptoms, it may be taken alongside antipyretics, expectorants, and analgesics.

Uses

A dietary supplement to support the immune system and help alleviate symptoms associated with various viral and bacterial infections, such as those caused by COVID-19 and MERS.
Depending on the stmptoms, it may be taken alongside antipyretics, expectorants, and analgesics.

Warnings

Do not use if you are sensitive to any of the ingredients in this product. Consult a healthcare professional before use if you are pregnant or breastfeeding.
Do not exceed the recommended dosage.
Swallow with sufficient water or a beverage to prevent aspiration.

Warnings

Keep out of reach of children
Pregnant women are advised to consult with their healthcare provider prior to use.

Warnings

Stop use and ask a doctor if symptoms persist or get worse.

Warnings

When using this product do not use more than directed.

take with enough water or drink to avoid getting into airway.

Warnings

Ensure that the included desiccant is not ingested.

Directions

For teenagers and adults (18+ years): Take 2 tablets once or twice daily.

For children aged 12-18 years: Take 1 tablet once daily.

For children aged 8-12 years: Take ½ tablet once daily.

Inactive Ingredients

Microcrystalline Cellulose, Lactose, Magnesium Oxide, Gardenia Florida Fruit Extract,Gardenia Jasminoides Fruit Extract, Maltodextrin, L-Phenylalanine, L-Leucine, L-Methionine, L-Lysine Hydrochloride, Palatinose, L-Isoleucine,Leucine,Isoleucine,Valine

Ascorbic Acid, Vitis Vinifera (Grape) Juice Powder, Flavor

Cyanocobalamin, Hydroxypropyl Methylcellulose, Phytonadione

Zinc Oxide, Corn Starch, Panax Ginseng Root Powder. Silica

Cholecalciferol, Silk Extract, Cordyceps Sinensis Extract, Nelumbo Nucifera (Lotus) Leaf Powder

Label

84540-502R Cos